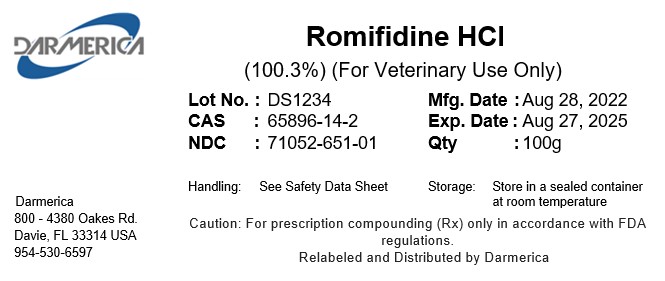 DRUG LABEL: Romifidine HCl
NDC: 71052-651 | Form: POWDER
Manufacturer: DARMERICA, LLC
Category: other | Type: BULK INGREDIENT - ANIMAL DRUG
Date: 20241223

ACTIVE INGREDIENTS: ROMIFIDINE HYDROCHLORIDE 1 kg/1 kg

Romifidine HCl